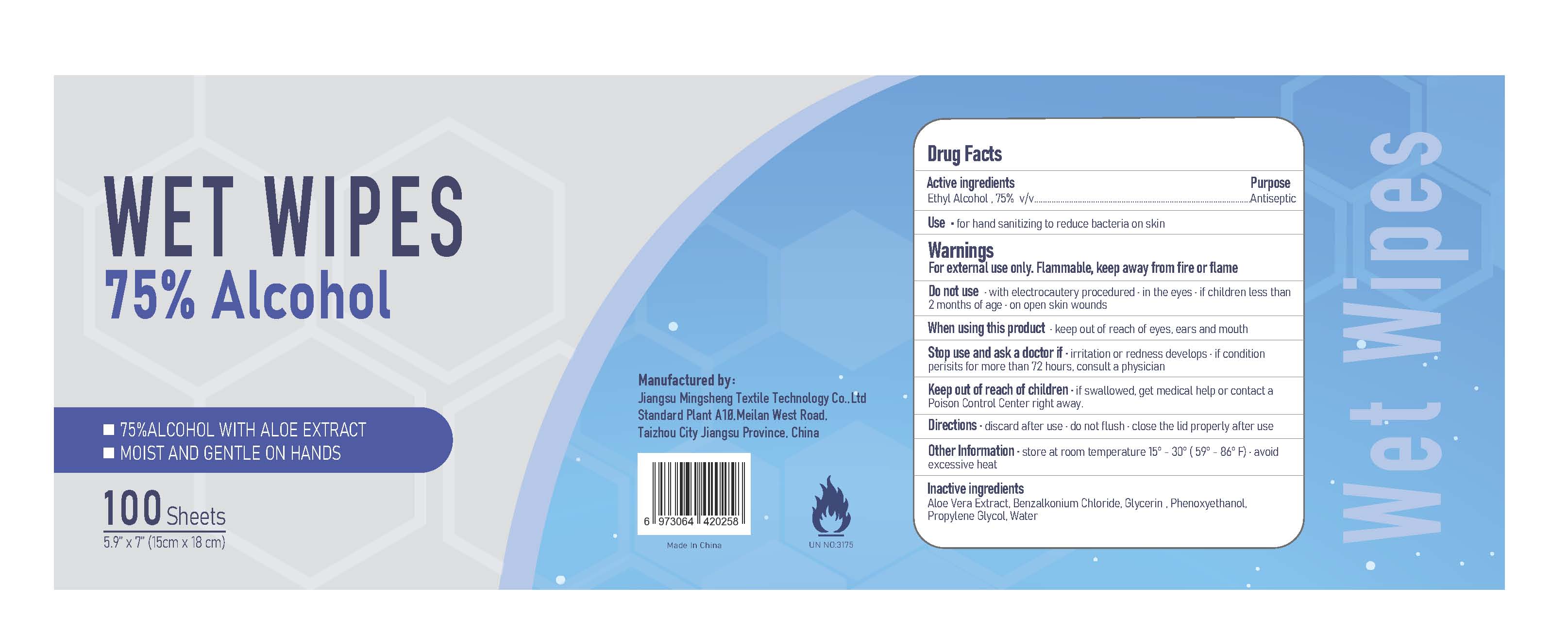 DRUG LABEL: WET WIPES
NDC: 90037-100 | Form: CLOTH
Manufacturer: Jiangsu Mingsheng Textile Technology Co., Ltd
Category: otc | Type: HUMAN OTC DRUG LABEL
Date: 20200821

ACTIVE INGREDIENTS: ALCOHOL 0.75 1/1 1
INACTIVE INGREDIENTS: PHENOXYETHANOL; GLYCERIN; PROPYLENE GLYCOL; WATER; ALOE VERA LEAF; BENZALKONIUM CHLORIDE

WET WIPES 75% Alcohol

Active ingredients

Ethyl Alcohol , 75% v/v

Purpose

Antiseptic

Use

- for hand sanitizing to reduce bacteria on skin

Warnings

For external use only. Flammable, keep away from fire or flame

Do not use

- with electrocautery procedured
- in the eyes
- if children less than 2 months of age
- on open skin wounds

When using this product

- keep out of reach of eyes, ears and mouth

Stop use and ask a doctor if

- irritation or redness develops
- if condition perisits for more than 72 hours, consult a physician

Keep out of reach of children

- if swallowed, get medical help or contact a Poison Control Center right away.

Directions

- discard after use
- do not flush
- close the lid properly after use

Other Information

- store at room temperature 15° - 30° (59° - 86° F)
- avoid excessive heat

Inactive ingredients

Aloe Vera Extract, Benzalkonium Chloride, Glycerin , Methyl Phenoxyethanol, Propylene Glycol, Water